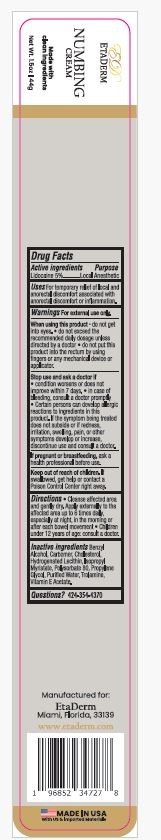 DRUG LABEL: ETADERM Numbing Cream
NDC: 84180-001 | Form: CREAM
Manufacturer: NUEPHASE LLC
Category: otc | Type: HUMAN OTC DRUG LABEL
Date: 20251224

ACTIVE INGREDIENTS: LIDOCAINE 5 g/100 g
INACTIVE INGREDIENTS: BENZYL ALCOHOL; CARBOMER; CHOLESTEROL; HYDROGENATED SOYBEAN LECITHIN; ISOPROPYL MYRISTATE; POLYSORBATE 80; PROPYLENE GLYCOL; WATER; TROLAMINE; .ALPHA.-TOCOPHEROL ACETATE

ETADERM Numbing Cream

Active Ingredients

Lidocaine 5 %

Purpose

Local Anesthetic

Uses:

For temporary relief of local and Anorectal discomfort associated with Anorectal discomfort or inflammation

Warnings:

For external use only

When using this product

- ▪ do not get into eyes. ▪ do not exceed the recommended daily dosage unless directed by a doctor ▪ do not put this product into the rectum by using fingers or any mechanical device or applicator.

Stop use and ask a doctor if

- ▪ condition worsens or does not improve within 7 days. ▪ in case of bleeding, consult a doctor promptly ▪ Certain persons can develop
  allergic reactions to ingredients in this product. If the symptom being treated does not subside or if redness, irritation, swelling, pain or other symptoms develop or increase, discontinue use and consult a doctor.

Keep out of reach of children.

If swallowed, get medical help or contact a Poison Control Center right away.

If pregnant or breast-feeding,

ask a health professional before use

Directions:

▪ Cleanse affected area and gently dry. Apply externally to the affected area up to 6 times daily, especially at night, in the morning or after each bowel movement ▪ Children under 12 years of age: consult a doctor.

Inactive Ingredients:

Benzyl Alcohol, Carbomer, Cholesterol, Hydrogenated Lecithin, Isopropyl Myristate, Polysorbate 80, Propylene Glycol, Purified Water, Trolamine, Vitamin E Acetate.

Questions?

424-354-4370